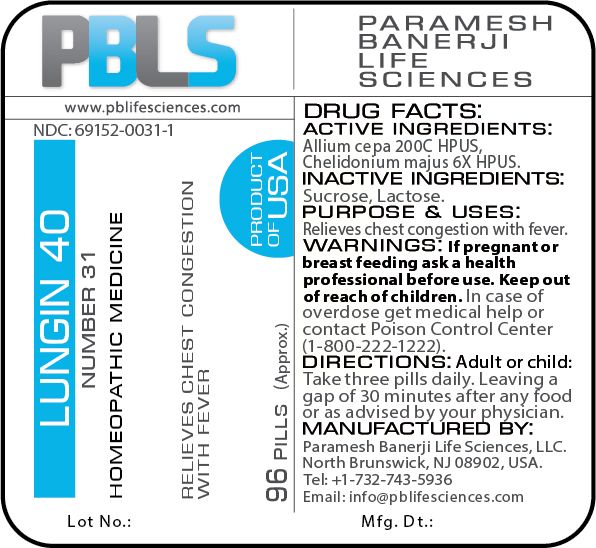 DRUG LABEL: Lungin 40 (Number 31)
NDC: 69152-0031 | Form: PELLET
Manufacturer: Paramesh Banerji Life Sciences LLC
Category: homeopathic | Type: HUMAN OTC DRUG LABEL
Date: 20180702

ACTIVE INGREDIENTS: CHELIDONIUM MAJUS 6 [hp_X]/1 1; ONION 200 [hp_C]/1 1
INACTIVE INGREDIENTS: SUCROSE; LACTOSE

DRUG FACTS: Active Ingredients

Allium cepa 200C HPUS, Chelidonium majus 6X HPUS

Inactive Ingredients

Sucrose, Lactose

Purpose

Relieves chest congestion with fever

Warnings

If pregnant or breast feeding ask a health professional before use.

Keep out of reach of children. In case of overdose, get medical help or contact a Poison Control Center (1-800-222-1222) right away.

Direction

Adult or child: Take three pills daily. Leaving a gap of 30 minutes after any food or as advised by your physician.

Manufactured by

Paramesh Banerji Life Sciences, LLC.

North Brunswick, NJ 08902, USA.

Tel: +1-732-743-5936

Email: info@pblifesciences.com

Principal Display Panel

NDC: 69152-0031-1

Lungin 40

Number 31

Homeopathic Medicine

Relieves chest congestion with fever

96 Pills (Approx.)

Product of USA